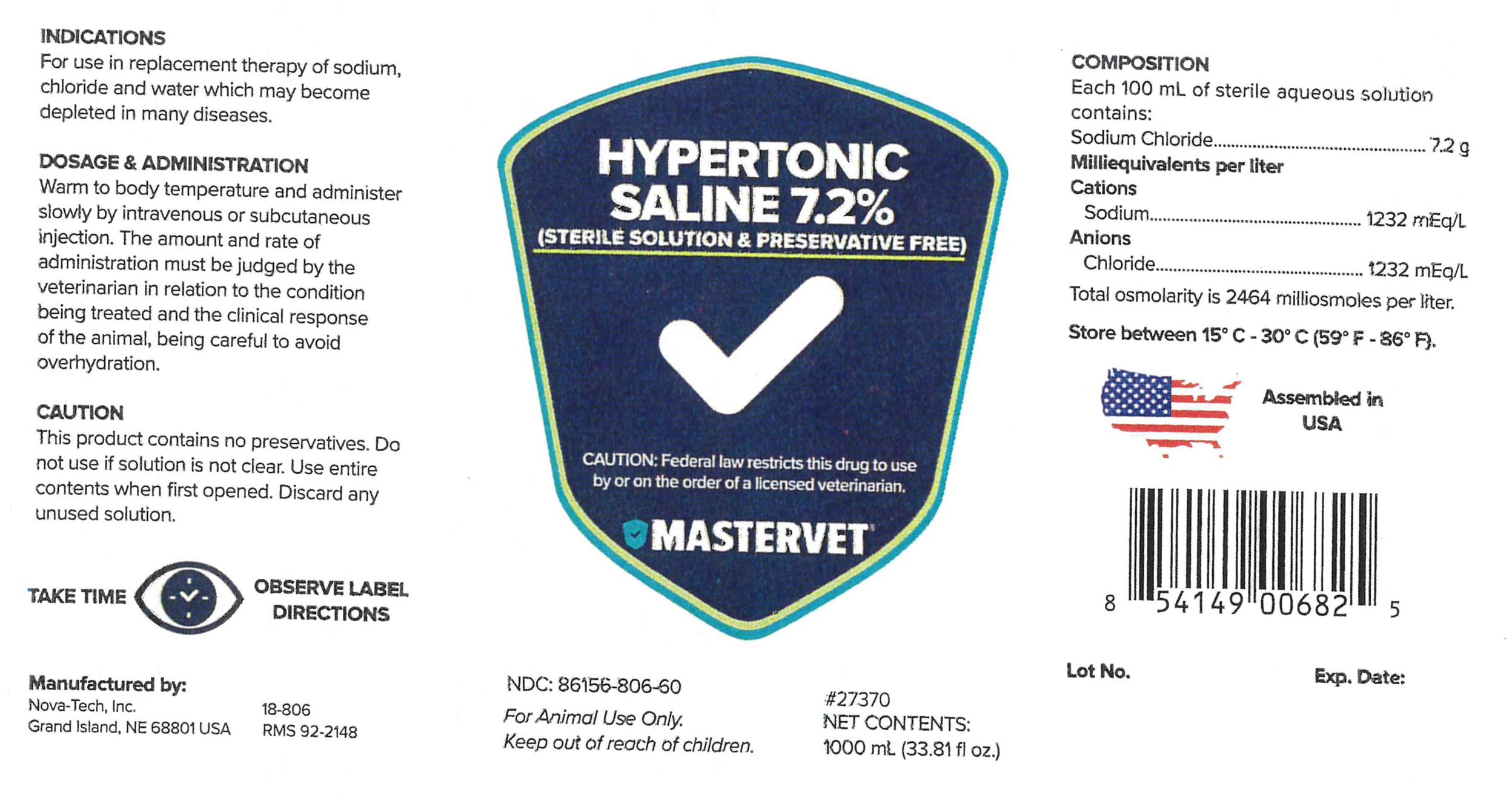 DRUG LABEL: Hypertonic Saline 7.2%
NDC: 86156-806 | Form: INJECTION, SOLUTION
Manufacturer: MasterVet
Category: animal | Type: PRESCRIPTION ANIMAL DRUG LABEL
Date: 20230109

ACTIVE INGREDIENTS: SODIUM CHLORIDE 7.2 g/100 mL

Hypertonic Saline 7.2%

Indications

For use in replacement therapy of sodium, chloride and water which may become depleted in many diseases.

Caution

This product contains no preservatives. Do not use if solution is not clear. Use entire contents when first opened. Discard any unused solution.

Dosage and Administration

Warm to body temperature and administer slowly by intravenous or subcutaneous injection. The amount and rate of administration must be judged by the veterinarian in relation to the condition being treated and the clinical response of the animal, being careful to avoid overhydration.

GENERAL PRECAUTIONS

Sterile Solution & Preservative Free

FOR ANIMAL USE ONLY.

KEEP OUT OF REACH OF CHILDREN.

CAUTION:

Federal law restricts this drug to use by or on the order of a licensed veterinarian.

Composition

Each 100 mL of sterile aqueous solution contains:
Sodium Chloride..........................7.2 g

Milliequivalents per liter

Cations
Sodium.............................1232 mEq/L
Anions
Chloride............................1232 mEq/L

Total osmolarity is 2464 milliosmoles per liter.

STORAGE AND HANDLING

Store between 15°C - 30°C (59°F - 86°F).

PRECAUTIONS

TAKE TIME OBSERVE LABEL DIRECTIONS

INFORMATION FOR OWNERS/CAREGIVERS

Manufactured by:

Nova-Tech, Inc.

Grand Island, NE 68801 USA

18-806
RMS 92-2148

NDC: 86156-806-60

#27370

Net Contents:

1000 mL (33.81 fl oz.)

Assembled in USA

Lot No. Exp. Date: